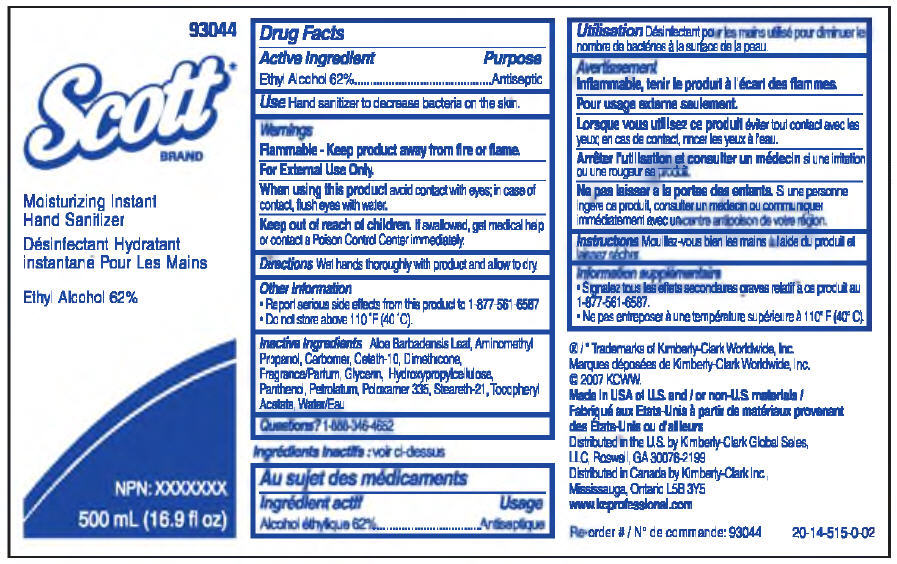 DRUG LABEL: Scott 
NDC: 55118-325 | Form: SOLUTION
Manufacturer: Kimberly-Clark Corporation
Category: otc | Type: HUMAN OTC DRUG LABEL
Date: 20141007

ACTIVE INGREDIENTS: Alcohol 62 mL/100 mL
INACTIVE INGREDIENTS: Water; Glycerin; Dimethicone; Petrolatum; Aminomethylpropanol; .ALPHA.-Tocopherol Acetate; Panthenol; Hydroxypropyl Cellulose (Type H); Ceteth-10; Steareth-21; Poloxamer 335; Aloe Vera Leaf

Scott Moisturizing Instant Hand Sanitizer

Drug Facts

Active Ingredient

Ethyl Alcohol 62%

Purpose

Antiseptic

Use

Hand sanitizer to decrease bacteria on the skin.

Warnings

Flammable - Keep product away from fire or flame.

For External Use Only.

When using this product avoid contact with eyes; in case of contact, flush eyes with water.

STOP USE

Stop use & ask a doctor if irritation or redness develops and persists.

Keep out of reach of children. If swallowed, get medical help or contact a Poison Control Center right away.

Directions

Wet hands thoroughly with product and allow to dry.

Other Information

- Report serious side effects from this product to 1-877-561-6587.
- Do not store above 110 °F (40 °C).

Inactive Ingredients

Aloe Barbadensis Leaf, Aminomethyl Propanol, Carbomer, Ceteth-10, Dimethicone, Fragrance, Glycerin, Hydroxypropylcellulose, Panthenol, Petrolatum, Poloxamer 335, Steareth-21, Tocopheryl Acetate, Water

Questions?

1-888-346-4652

Distributed in the U.S. by Kimberly-Clark Global Sales, LLC,
Roswell, GA 30076-2199

PRINCIPAL DISPLAY PANEL - 500 mL Bottle Label

93044

Scott*
BRAND

Moisturizing Instant
Hand Sanitizer

Ethyl Alcohol 62%

NPN: XXXXXXX

500 mL (16.9 fl oz)